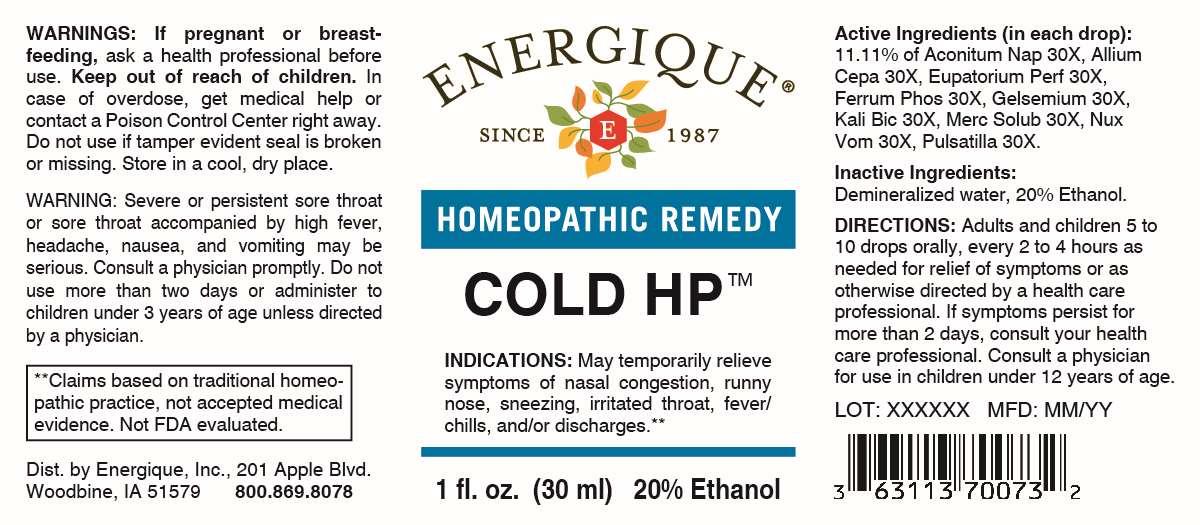 DRUG LABEL: Cold HP
NDC: 44911-0089 | Form: LIQUID
Manufacturer: Energique, Inc.
Category: homeopathic | Type: HUMAN OTC DRUG LABEL
Date: 20241024

ACTIVE INGREDIENTS: ACONITUM NAPELLUS WHOLE 30 [hp_X]/1 mL; ONION 30 [hp_X]/1 mL; EUPATORIUM PERFOLIATUM FLOWERING TOP 30 [hp_X]/1 mL; FERRUM PHOSPHORICUM 30 [hp_X]/1 mL; GELSEMIUM SEMPERVIRENS ROOT 30 [hp_X]/1 mL; POTASSIUM DICHROMATE 30 [hp_X]/1 mL; MERCURIUS SOLUBILIS 30 [hp_X]/1 mL; STRYCHNOS NUX-VOMICA SEED 30 [hp_X]/1 mL; PULSATILLA VULGARIS 30 [hp_X]/1 mL
INACTIVE INGREDIENTS: WATER; ALCOHOL

DRUG FACTS:

ACTIVE INGREDIENTS:

(in each drop): 11.11% of Aconitum Napellus 30X, Allium Cepa 30X, Eupatorium Perfoliatum 30X, Ferrum Phosphoricum 30X, Gelsemium Sempervirens 30X, Kali Bichromicum 30X, Mercurius Solubilis 30X, Nux Vomica 30X, Pulsatilla 30X.

PURPOSE:

May temporarily relieve symptoms of nasal congestion, runny nose, sneezing, irritated throat, fever/chills, and/or discharges.**

**Claims based on traditional homeopathic practice, not accepted medical evidence. Not FDA evaluated.

WARNINGS:

If pregnant or breast-feeding, ask a health professional before use.

Keep out of reach of children. In case of overdose, get medical help or contact a Poison Control Center right away.

Do not use if tamper evident seal is broken or missing.

Store in a cool, dry place.

Severe or persistent sore throat or sore throat accompanied by fever, headache, nausea, and vomiting may be serious. Consult a physician promptly. Do not use more than two days or administer to children under 3 years of age unless directed by a physician.

DIRECTIONS:

Adults and children 5 to 10 drops orally, every 2 to 4 hours as needed for relief of symptoms or as otherwise directed by a health care professional. If symptoms persist for more than 2 days, consult your health care professional. Consult a physician for use in children under 12 years of age.

INACTIVE INGREDIENTS:

Demineralized water, 20% Ethanol.

KEEP OUT OF REACH OF CHILDREN:

In case of overdose, get medical help or contact a Poison Control Center right away.

INDICATIONS:

May temporarily relieve symptoms of nasal congestion, runny nose, sneezing, irritated throat, fever/chills, and/or discharges.**

**Claims based on traditional homeopathic practice, not accepted medical evidence. Not FDA evaluated.

QUESTIONS:

Dist. By Energique, Inc.

201 Apple Blvd.

Woodbine, IA 51579

800.869.8078

PACKAGE DISPLAY LABEL:

ENERGIQUE

SINCE 1987

HOMEOPATHIC REMEDY

COLD HP

1 fl. oz. (30 ml)